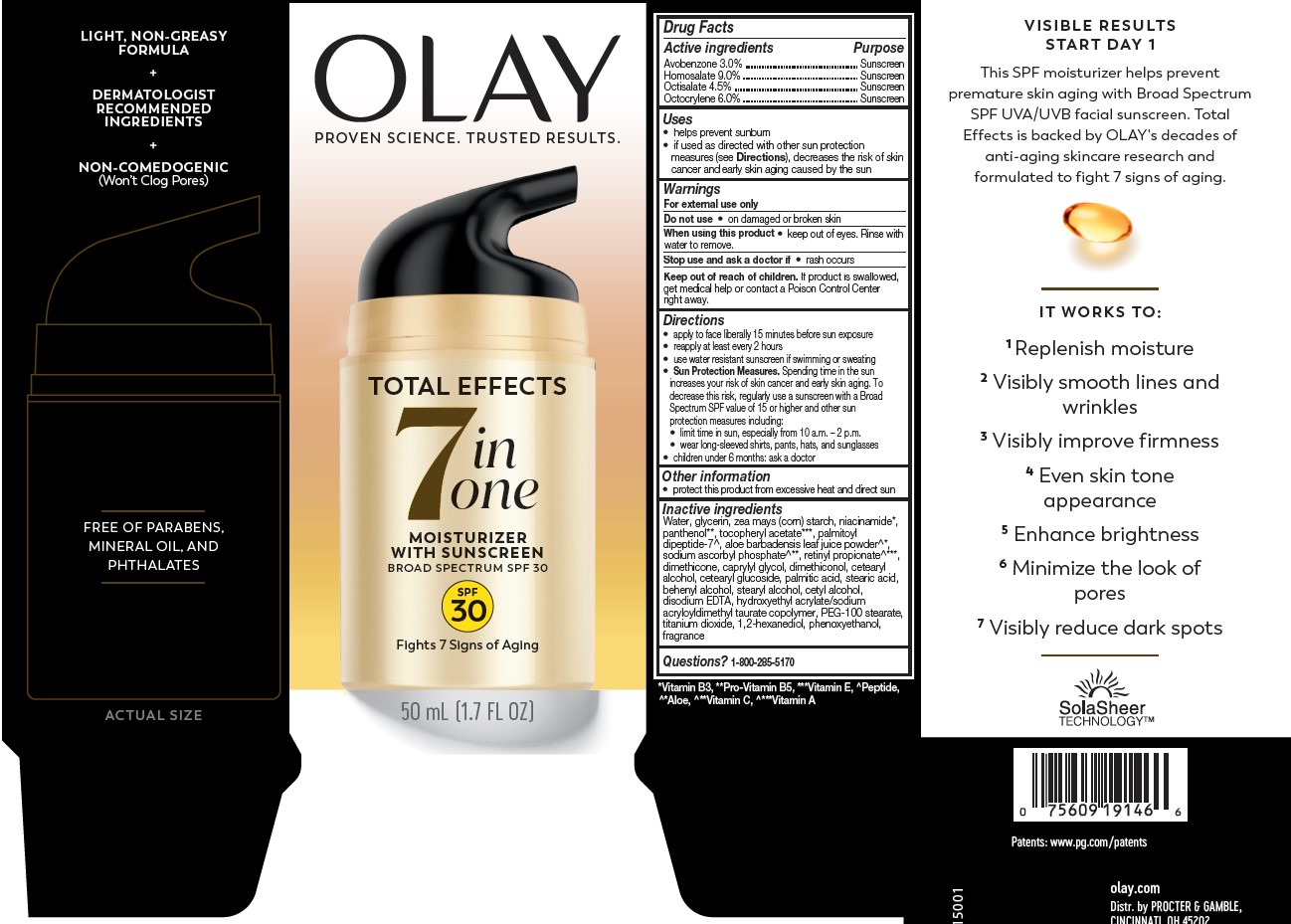 DRUG LABEL: Olay Total Effects Moisturizer
NDC: 69423-389 | Form: LOTION
Manufacturer: The Procter & Gamble Manufacturing Company
Category: otc | Type: HUMAN OTC DRUG LABEL
Date: 20250819

ACTIVE INGREDIENTS: AVOBENZONE 3 g/100 mL; HOMOSALATE 9 g/100 mL; OCTISALATE 4.5 g/100 mL; OCTOCRYLENE 6 g/100 mL
INACTIVE INGREDIENTS: ALOE BARBADENSIS LEAF POWDER; DIMETHICONOL (50000 CST); PALMITOYL DIPEPTIDE-7; PHENOXYETHANOL; HYDROXYETHYL ACRYLATE/SODIUM ACRYLOYLDIMETHYL TAURATE COPOLYMER (100000 MPA.S AT 1.5%); RETINYL PROPIONATE; GLYCERIN; SODIUM ASCORBYL PHOSPHATE; PALMITIC ACID; WATER; NIACINAMIDE; .ALPHA.-TOCOPHEROL ACETATE; PANTHENOL; DIMETHICONE; STEARYL ALCOHOL; BEHENYL ALCOHOL; PEG-100 STEARATE; CETYL ALCOHOL; CETEARYL GLUCOSIDE; CETEARYL ALCOHOL; STEARIC ACID; EDETATE DISODIUM; TITANIUM DIOXIDE; CAPRYLYL GLYCOL; 1,2-HEXANEDIOL

Olay® Total Effects® Moisturizer
Broad Spectrum SPF 30

Drug Facts

Active ingredients
Avobenzone 3.0%
Homosalate 9.0%
Octisalate 4.5%
Octocrylene 6.0%

PURPOSE

Sunscreen

Uses

- helps prevent sunburn
- if used as directed with other sun protection measures (see Directions), decreases the risk of skin cancer and early skin aging caused by the sun

Warnings

For external use only

Do not use on damaged or broken skin

When using this product keep out of eyes.
Rinse with water to remove.

Stop use and ask a doctor if rash occurs

Keep out of reach of children. If product is swallowed, get medical help or contact a Poison Control Center right away.

Directions

- apply liberally 15 minutes before sun exposure
- reapply at least every 2 hours
- use water resistant sunscreen if swimming or sweating
- Sun Protection Measures. Spending time in the sun increases your risk of skin cancer and early skin aging. To decrease this risk, regularly use a sunscreen with a Broad Spectrum SPF value of 15 or higher and other sun protection measures including:
  - limit time in sun, especially from 10 a.m. – 2 p.m.
  - wear long-sleeved shirts, pants, hats, and sunglasses
- children under 6 months: ask a doctor

Other information

- protect this product from excessive heat and direct sun

Inactive ingredients

Water, glycerin, zea mays (corn) starch, niacinamide, panthenol, tocopheryl acetate,palmitoyl dipeptide-7, aloe barbadensis leaf juice powder, sodium ascorbyl phosphate, retinyl propionate, dimethicone, caprylyl glycol, dimethiconol, cetearyl alcohol, cetearyl glucoside, palmitic acid, stearic acid, behenyl alcohol, stearyl alcohol, cetyl alcohol, disodium EDTA, hydroxyethyl acrylate/sodium acryloyldimethyl taurate copolymer, PEG-100 stearate, titanium dioxide, 1,2-hexanediol, phenoxyethanol, fragrance

Questions or comments?

Call 1-800-285-5170

Distr. by PROCTER & GAMBLE,
CINCINNATI, OH 45202

PRINCIPAL DISPLAY PANEL - 50 mL Bottle Carton

OLAY®

TOTAL EFFECTS

7 IN

ONE

MOISTURIZER

WITH SUNSCREEN

BROAD SPECTRUM SPF 30
50 mL (1.7 FL OZ)